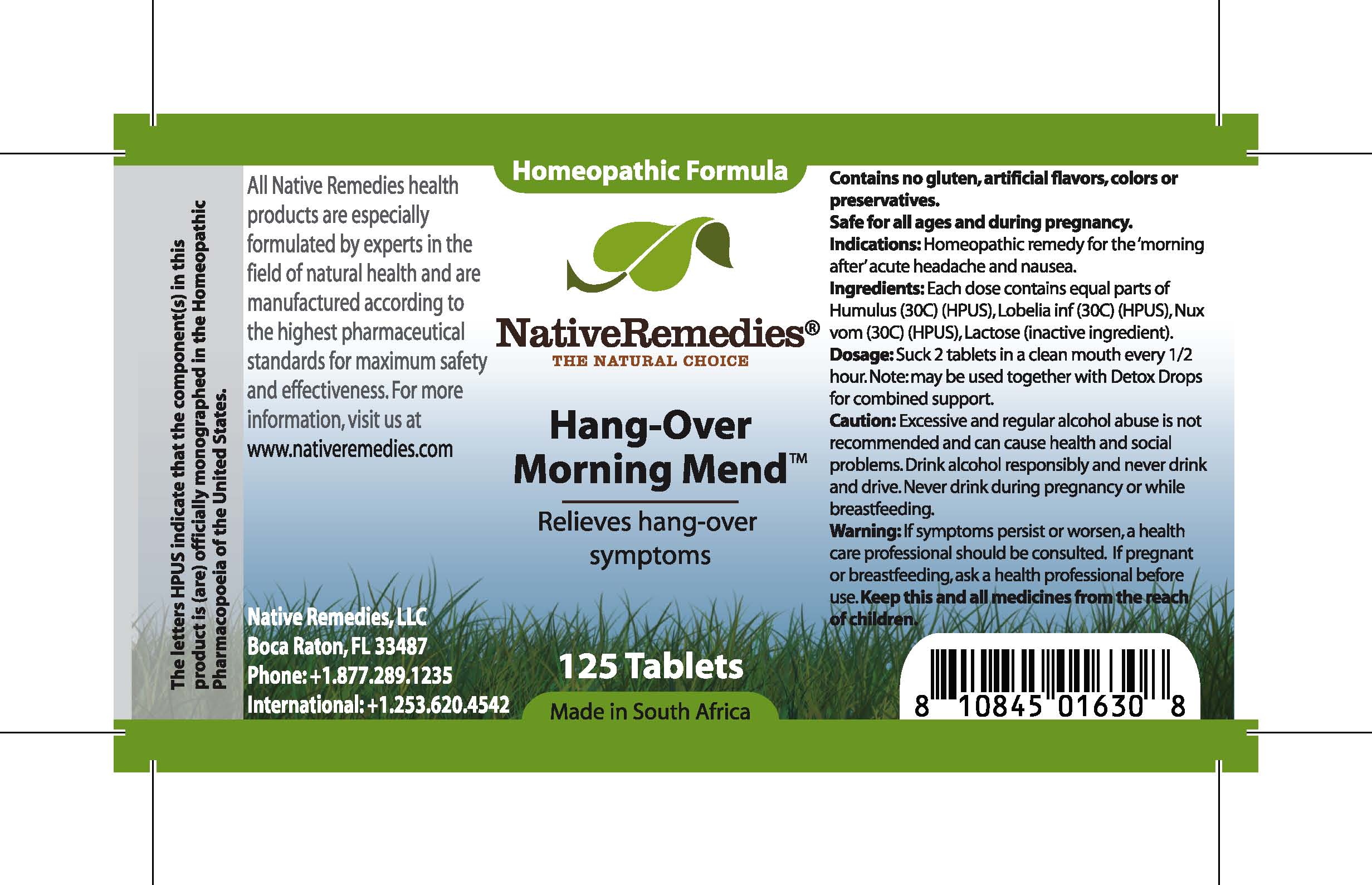 DRUG LABEL: Hang-Over Morning Mend
NDC: 68647-112 | Form: TABLET
Manufacturer: Feelgood Health
Category: homeopathic | Type: HUMAN OTC DRUG LABEL
Date: 20100715

ACTIVE INGREDIENTS: HOPS 30 [hp_C]/1 1; LOBELIA 30 [hp_C]/1 1; STRYCHNOS NUX-VOMICA SEED 30 [hp_C]/1 1
INACTIVE INGREDIENTS: LACTOSE

Hang-Over Morning Mend

DESCRIPTION

Relieves hang-over symptoms

INDICATIONS AND USAGE

Indications: Homeopathic remedy for the ‘morning after’ acute headache and nausea.

DOSAGE AND ADMINISTRATION

Dosage: Dissolve 2 tablets in a clean mouth every 1/2 hour. May be used together with Detox Drops™ for combined support.

GENERAL PRECAUTIONS

Caution: Excessive and regular alcohol abuse is not recommended and can cause health and social problems. Drink alcohol responsibly and never drink and drive. If symptoms persist or worsen, a health care professional should be consulted. Keep this and all medicines from the reach of children.

ACTIVE INGREDIENT

Ingredients: Each dose contains equal parts of Humulus (30C) (HPUS), Lobelia inf (30C) (HPUS), Nux vom (30C) (HPUS)

Lactose (inactive ingredient).

PREGNANCY

If pregnant or breastfeeding, ask a health professional before use. Never drink during pregnancy or while breastfeeding.

USER SAFETY WARNINGS

Contains no gluten, artificial flavors, colors or preservatives. Safe for all ages and during pregnancy.

PATIENT COUNSELING INFORMATION

All Native Remedies health products are especially formulated by experts in the field of natural health and are manufactured according to the highest pharmaceutical standards for maximum safety and effectiveness. For more information, visit us at www.nativeremedies.com

Distributed by

Native Remedies, LLC

6531 Park of Commerce Blvd.

Suite 160

Boca Raton, FL 33487

Phone: 1.877.289.1235

International: + 1.561.999.8857

The letters HPUS indicate that the component(s) in this product is (are) officially monographed in the Homeopathic Pharmacopoeia of the United States.